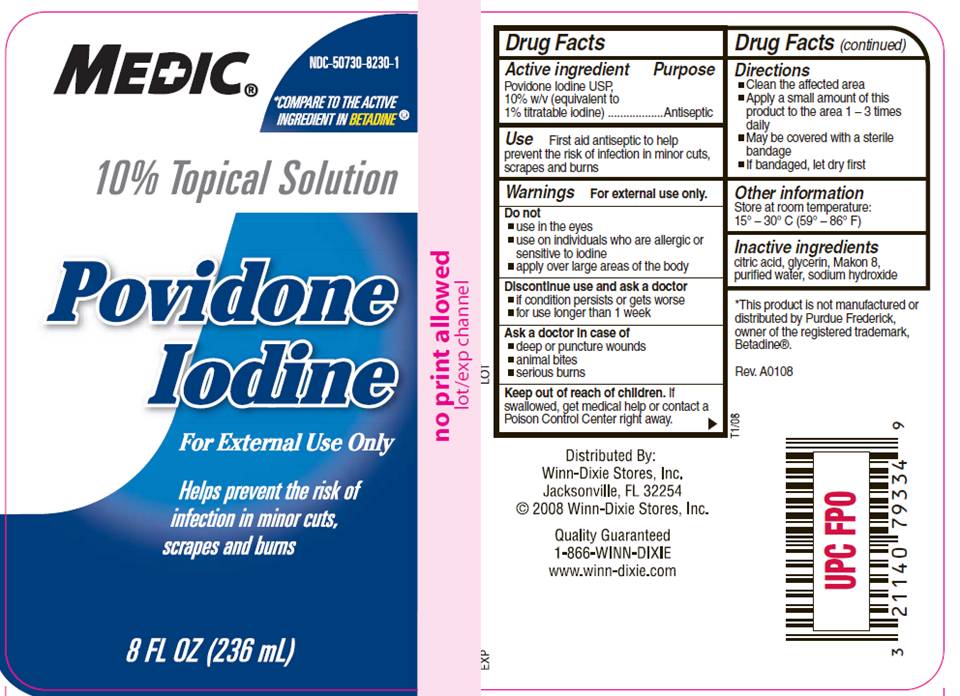 DRUG LABEL: Povidone Iodine
NDC: 50730-8230 | Form: SOLUTION
Manufacturer: Triad Group
Category: otc | Type: HUMAN OTC DRUG LABEL
Date: 20100222

ACTIVE INGREDIENTS: povidone-iodine 0.10 mg/1 mL
INACTIVE INGREDIENTS: citric acid monohydrate; glycerin; sodium hydroxide; water

DRUG FACTS

ACTIVE INGREDIENT

Povidone Iodine,10% w/v (equivalent to 1% titratable iodine)

PURPOSE

Antiseptic

USE

First aid antiseptic to help prevent the risk of infection in minor cuts, scrapes and burns

WARNINGS

For external use only.

Do not

- use in the eyes
- use on individuals who are allergic or sensitive to iodine
- apply over large areas of the body

Discontinue use and ask a doctor

- if condition persists or gets worse
- for use longer than 1 week

Ask a doctor in case of

- deep or puncture wounds
- animal bites
- serious burns

Keep out of reach of children

If swallowed, get medical help or contact a Poison Control Center right away.

DIRECTIONS

- Clean the affected area
- Apply a small amount of this product to the area 1-3 times daily
- May be covered with a sterile bandage
- If bandaged, let dry first

OTHER INFORMATION

Store at room temperature 15° - 30° C (59° - 86° F)

INACTIVE INGREDIENTS

citric acid, glycerin, Makon 8, purified water, sodium hydroxide

PACKAGE INFORMATION

MEDIC®

NDC 50730-8230-1

*COMPARE TO THE ACTIVE
INGREDIENT IN BETADINE®

10% Topical Solution
Povidone
Iodine
For External Use Only
Helps prevent the risk of
infection in minor cuts,
scrapes and burns
8 FL OZ (236 mL)
Distributed by Winn-Dixie Stores, Inc.
Jacksonville, FL 32254
©2008 Winn-Dixie Stores, Inc.
Quality Guaranteed
1-866-WINN-DIXIE
www.winn-dixie.com
*This product is not manufactured or distributed by Purdue Frederick, owner of the registered trademark, Betadine®.